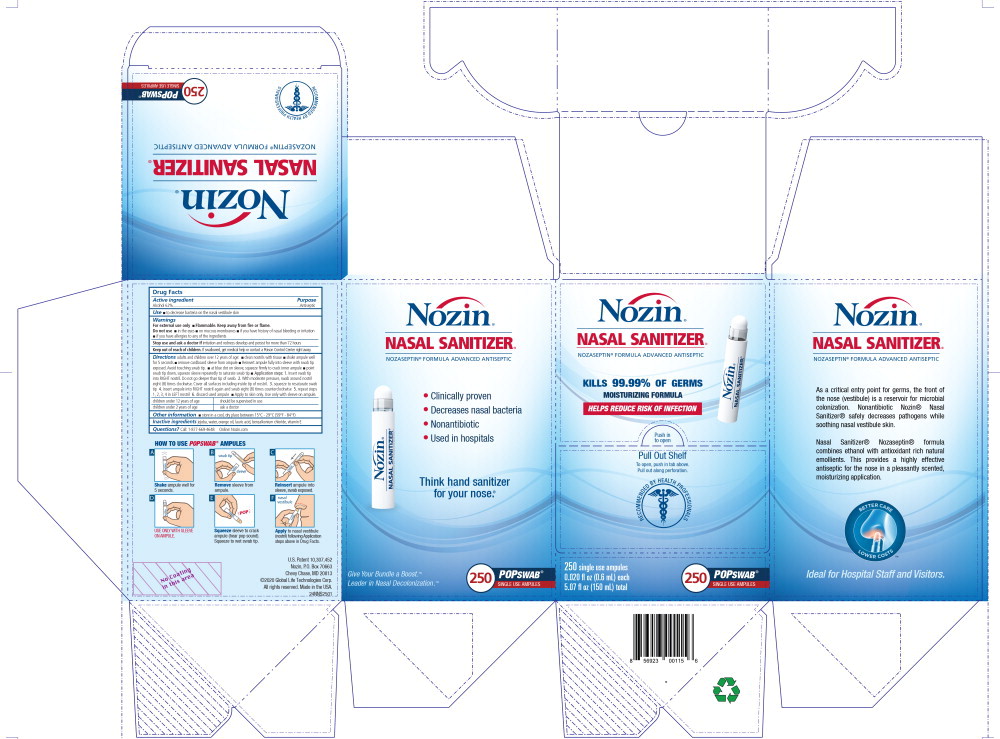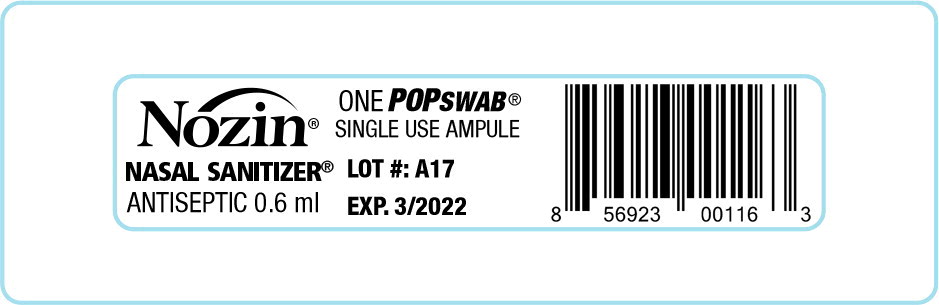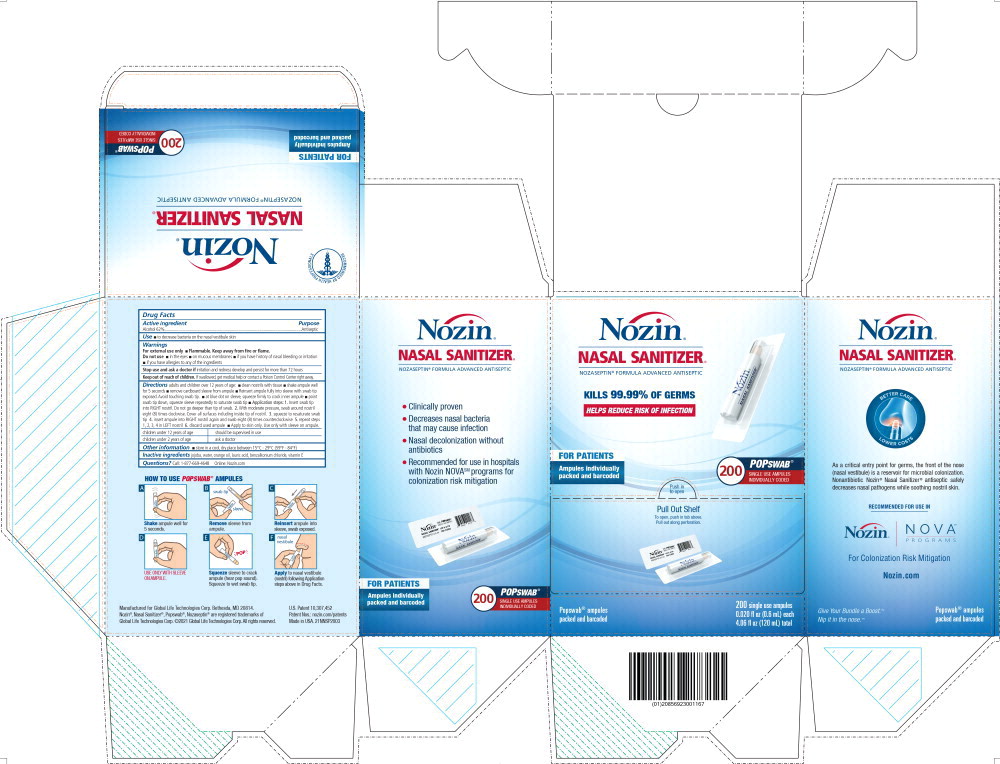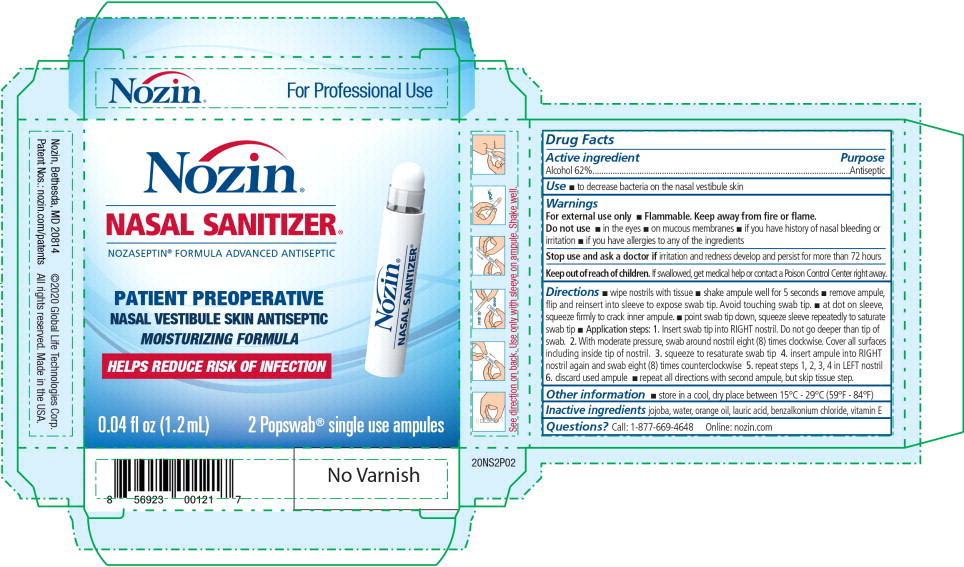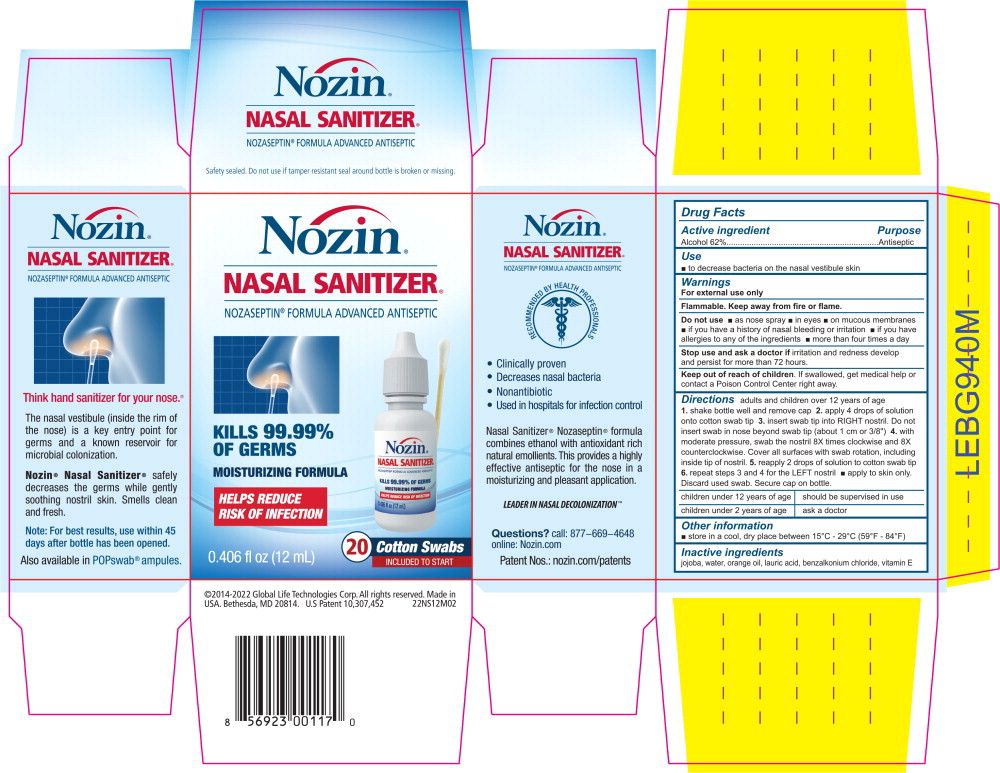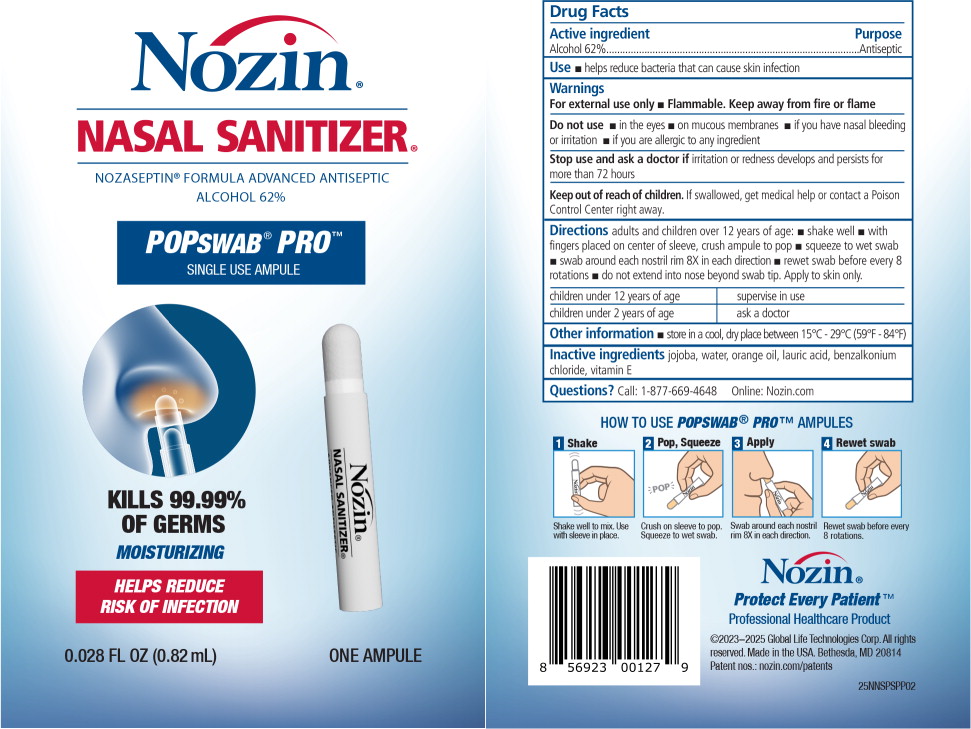 DRUG LABEL: Nozin Nasal Sanitizer (Antiseptic)
NDC: 82539-211 | Form: LIQUID
Manufacturer: Global Life Technologies Corp. 
Category: otc | Type: HUMAN OTC DRUG LABEL
Date: 20250505

ACTIVE INGREDIENTS: Alcohol 62 mL/100 mL
INACTIVE INGREDIENTS: jojoba oil; water; orange oil; lauric acid; benzalkonium chloride; .alpha.-tocopherol acetate

Drug Facts

Active ingredient

Alcohol 62%

Purpose

Antiseptic

Use

- to decrease bacteria on the nasal vestibule skin

Warnings

For external use only

- Flammable. Keep away from fire or flame.

Do not use

- in the eyes
- on mucous membranes
- if you have history of nasal bleeding or irritation
- if you have allergies to any of the ingredients

Stop use and ask a doctor if irritation and redness develop and persist for more than 72 hours

Keep out of reach of children. If swallowed, get medical help or contact a Poison Control Center right away.

Directions

- wipe nostrils with tissue
- shake ampule well for 5 seconds
- remove ampule, flip and reinsert into sleeve to expose swab tip. Avoid touching swab tip.
- at dot on sleeve, squeeze firmly to crack inner ampule.
- point swab tip down, squeeze sleeve repeatedly to saturate swab tip
- Application steps: 1. Insert swab tip into RIGHT nostril. Do not go deeper than tip of swab. 2. With moderate pressure, swab around nostril eight (8) times clockwise. Cover all surfaces including inside tip of nostril. 3. squeeze to resaturate swab tip 4. insert ampule into RIGHT nostril again and swab eight (8) times counterclockwise 5. repeat steps 1, 2, 3, 4 in LEFT nostril 6. discard used ampule
- repeat all directions with second ampule, but skip tissue step.

Other information

- store in a cool, dry place between 15°C - 29°C (59°F - 84°F)

Inactive ingredients

jojoba, water, orange oil, lauric acid, benzalkonium chloride, vitamin E

Questions?

Call: 1-877-669-4648 Online: nozin.com

Principal Display Panel – 0.6 mL Carton Label

Nozin®

NASAL SANITIZER®

NOZASEPTIN® FORMULA ADVANCED ANTISEPTIC

KILLS 99.99% OF GERMS

MOISTURIZING FORMULA

HELPS REDUCE RISK OF INFECTION

Push in
to open

Pull Out Shelf

To open, push in tab above.
Pull out along perforation.

RECOMMENDED BY HEALTH PROFFESSIONALS

250 single use ampules
0.020 fl oz (0.6 mL) each
5.07 fl oz (150 mL) total

250 POPSWAB®
SINGLE USE AMPULES

Principal Display Panel – 0.6 mL Carton Label

Nozin®

NASAL SANITIZER®

ANTISEPTIC 0.6 ml

ONE POPSWAB®

SINGLE USE AMPULE

Principal Display Panel – 0.6 mL Carton Label

Nozin®

NASAL SANITIZER®

NOZASEPTIN® FORMULA ADVANCED ANTISEPTIC

KILLS 99.99% OF GERMS

HELPS REDUCE RISK OF INFECTION

FOR PATIENTS
Ampules individually
packed and barcoded

Push in
to open

Pull Out Shelf

To open, push in tab above.
Pull out along perforation.

Popswab® ampules
packed and barcoded

200 single use ampules
0.020 fl oz (0.6 mL) each
4.06 fl oz (120 mL) total

Principal Display Panel – 0.6 mL Carton Label

Nozin®

NASAL SANITIZER®

NOZASEPTIN® FORMULA ADVANCED ANTISEPTIC

PATIENT PREOPERATIVE
NASAL VESTIBULE SKIN ANTISEPTIC
MOISTURIZING FORMULA

HELPS REDUCE RISK OF INFECTION

0.04 fl oz (1.2 mL)

2 Popswab® single use ampules

Principal Display Panel – 12 mL Carton Label

Nozin®

NASAL SANITIZER®

NOZASEPTIN® FORMULA ADVANCED ANTISEPTIC

KILLS 99.99% OF GERMS

MOISTURIZING FORMULA

HELPS REDUCE RISK OF INFECTION

0.406 fl oz (12 mL)

20 COTTON SWABS

INCLUDED TO START

Principal Display Panel - 0.82 mL Pouch Label

Nozin®

NASAL SANITIZER®

NOZASEPTIN® FORMULA ADVANCED ANTISEPTIC

ALCOHOL 62%

POPSWAB® PRO™
SINGLE USE AMPULE

KILLS 99.99%
OF GERMS

MOISTURIZING

HELPS REDUCE
RISK OF INFECTION

0.028 FL OZ (0.82 mL)

ONE AMPULE